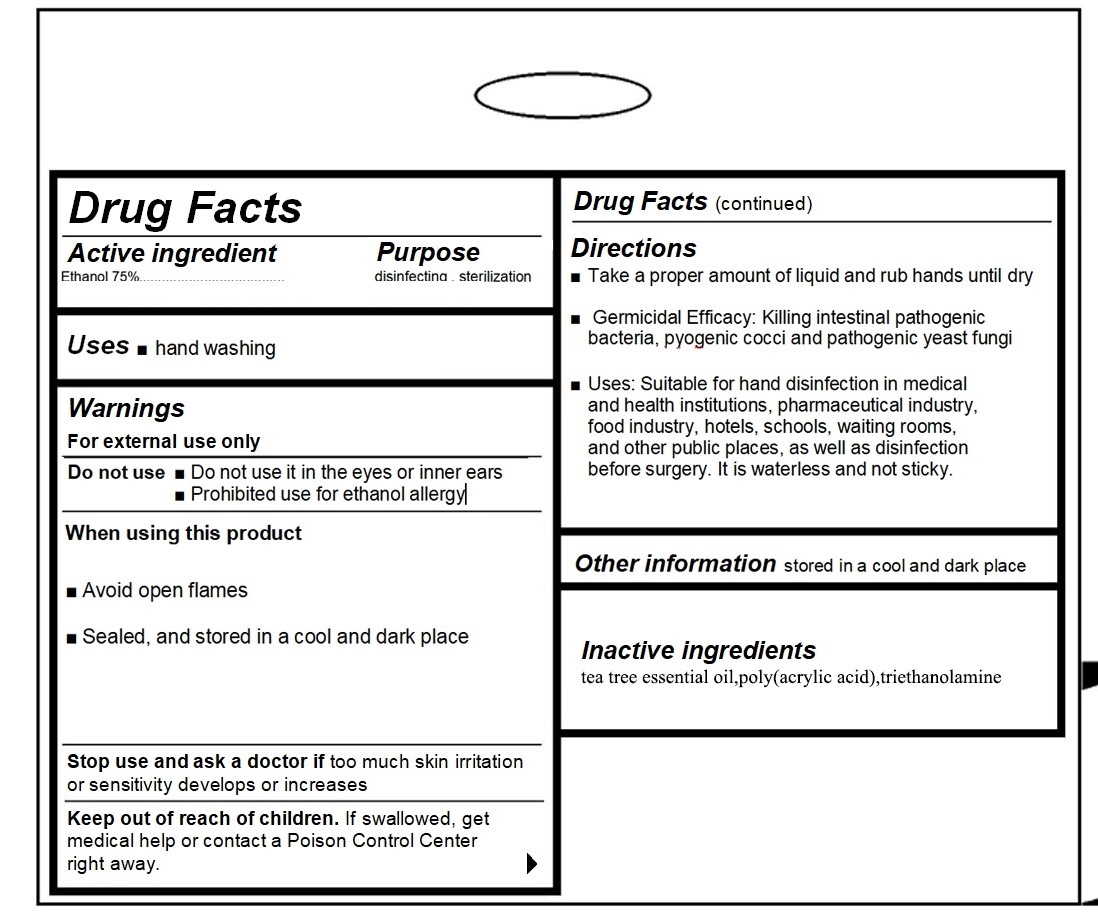 DRUG LABEL: waterless antibacteria hand sanitizer
NDC: 70876-003 | Form: LIQUID
Manufacturer: Fujian Meigulin Bio-Technique Co., Ltd.
Category: otc | Type: HUMAN OTC DRUG LABEL
Date: 20200420

ACTIVE INGREDIENTS: ALCOHOL 75 mL/100 mL
INACTIVE INGREDIENTS: WATER; MELALEUCA ALTERNIFOLIA LEAF; TROLAMINE; POLYACRYLIC ACID (250000 MW)

70876-003 hand sanitizer

Active ingredient

Ethanol 75%

Purpose

disinfecting , sterilization

Uses

hand washing

Warnings

For external use only
Do not use■Do not use it in the eyes or inner ears
■Prohibited use for ethanol allergy|
When using this product
s Avoid open flames
■Sealed, and stored in a cool and dark place
Stop use and ask a doctor if too much skin rritation
or sensitivity develops or increases

Keep out of reach of children. If swallowed, get
medical help or contact a Poison Control Center
right away.

Directions

n Take a proper amount of liquid and rub hands until dry
■Germicidal Efficacy: Klling intestinal pathogenic
bacteria, pyogenic cocci and pathogenic yeast fungi
■Uses: Suitable for hand disinfection in medical
and health institutions, pharmaceutical industry,
food industry, hotels, schools, waiting rooms,
and other public places, as well as disinfection
before surgery. It is waterless and not sticky.

INACTIVE INGREDIENT

Melaleuca alternifolia (tea tree essential oil) ，poly(acrylic acid)，Triethanolamine